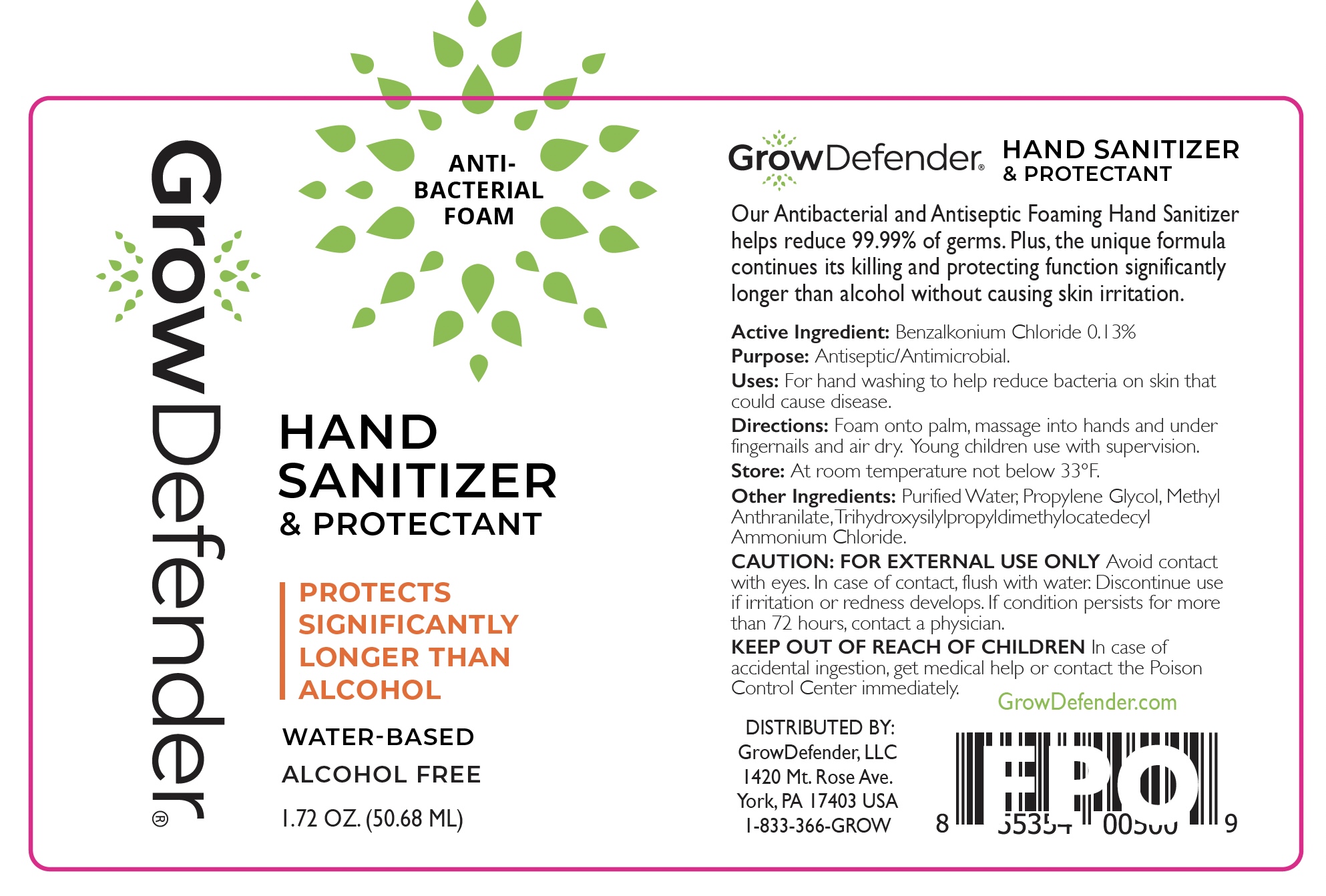 DRUG LABEL: GrowDefender Antibacterial Foam
NDC: 87109-0013 | Form: SOLUTION
Manufacturer: Grow Defender LLC
Category: otc | Type: HUMAN OTC DRUG LABEL
Date: 20251028

ACTIVE INGREDIENTS: BENZALKONIUM CHLORIDE 1.3 mg/1 mL
INACTIVE INGREDIENTS: WATER; PROPYLENE GLYCOL

Active Ingredient

Benzalkonium Chloride 0.13%

Purpose

Antiseptic / Antimicrobial

Uses

For hand washing to help reduce bacteria on skin that could cause disease.

Directions

Foam onto palm, massage into hands and under fingernails and air dry. Young children use with supervision.

Store

At room temperature not below 33°F.

Other Ingredients

Purified Water, Propylene Glycol, Methyl Anthranilate, Trihydroxysilylpropyldimethylocatedecyl Ammonium Chloride.

CAUTION

FOR EXTERNAL USE ONLY Avoid contact with eyes. In case of contact, flush with water. Discontinue use if irritation or redness develops. If condition persists for more than 72 hours, contact a physician.

KEEP OUT OF REACH OF CHILDREN

In case of accidental ingestion, get medical help or contact the Poison Control Center immediately.

PACKAGE LABEL

Antibacterial Foam

Hand Sanitizer & Protectant

Protects Significantly Longer than Alcohol

Water-Based

Alcohol Free